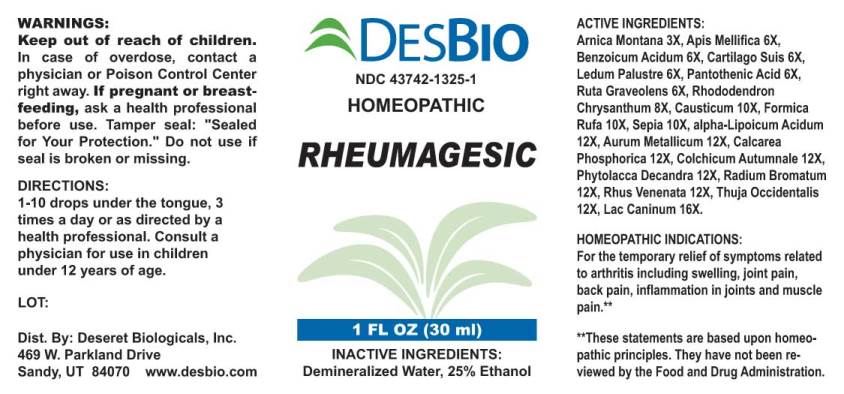 DRUG LABEL: Rheumagesic
NDC: 43742-1325 | Form: LIQUID
Manufacturer: Deseret Biologicals, Inc.
Category: homeopathic | Type: HUMAN OTC DRUG LABEL
Date: 20210113

ACTIVE INGREDIENTS: ARNICA MONTANA 3 [hp_X]/1 mL; APIS MELLIFERA 6 [hp_X]/1 mL; BENZOIC ACID 6 [hp_X]/1 mL; SUS SCROFA CARTILAGE 6 [hp_X]/1 mL; RHODODENDRON TOMENTOSUM LEAFY TWIG 6 [hp_X]/1 mL; PANTOTHENIC ACID 6 [hp_X]/1 mL; RUTA GRAVEOLENS FLOWERING TOP 6 [hp_X]/1 mL; RHODODENDRON AUREUM LEAF 8 [hp_X]/1 mL; CAUSTICUM 10 [hp_X]/1 mL; FORMICA RUFA 10 [hp_X]/1 mL; SEPIA OFFICINALIS JUICE 10 [hp_X]/1 mL; THIOCTIC ACID 12 [hp_X]/1 mL; GOLD 12 [hp_X]/1 mL; TRIBASIC CALCIUM PHOSPHATE 12 [hp_X]/1 mL; COLCHICUM AUTUMNALE BULB 12 [hp_X]/1 mL; PHYTOLACCA AMERICANA ROOT 12 [hp_X]/1 mL; RADIUM BROMIDE 12 [hp_X]/1 mL; TOXICODENDRON VERNIX LEAFY TWIG 12 [hp_X]/1 mL; THUJA OCCIDENTALIS LEAFY TWIG 12 [hp_X]/1 mL; CANIS LUPUS FAMILIARIS MILK 16 [hp_X]/1 mL
INACTIVE INGREDIENTS: WATER; ALCOHOL

Drug Facts:

ACTIVE INGREDIENTS:

Arnica Montana 3X, Apis Mellifica 6X, Benzoicum Acidum 6X, Cartilago Suis 6X, Ledum Palustre 6X, Pantothenic Acid 6X, Ruta Graveolens 6X, Rhododendron Chrysanthum 8X, Causticum 10X, Formica Rufa 10X, Sepia 10X, alpha-Lipoicum Acidum 12X, Aurum Metallicum 12X, Calcarea Phosphorica 12X, Phytolacca Decandra 12X, Radium Bromatum 12X, Rhus Venenata 12X, Thuja Occidentalis 12X, Lac Caninum 16X.

HOMEOPATHIC INDICATIONS:

For temporary relief of symptoms related to arthritis including swelling, joint pain, back pain, inflammation in joints and muscle pain. **

**These statements are based upon homeopathic principles. They have not been reviewed by the Food and Drug Administration.

WARNINGS:

Keep out of reach of children. In case of overdose, contact physician or a Poison Control Center right away.

If pregnant or breast-feeding, ask a health professional before use.

Tamper seal: "Sealed for Your Protection." Do not use if seal is broken or missing.

Keep out of reach of children. In case of overdose, contact physician or a Poison Control Center right away.

DIRECTIONS:

1-10 drops under the tongue, 3 times a day or as directed by a health professional. Consult a physician for use in children under 12 years of age.

HOMEOPATHIC INDICATIONS:

For temporary relief of symptoms related to arthritis including swelling, joint pain, back pain, inflammation in joints and muscle pain. **

**These statements are based upon homeopathic principles. They have not been reviewed by the Food and Drug Administration.

INACTIVE INGREDIENTS:

Demineralized Water, 25% Ethanol.

QUESTIONS:

Dist. By: Deseret Biologicals, Inc.

469 W. Parkland Drive

Sandy, UT 84070 www.desbio.com

PACKAGE LABEL DISPLAY:

DESBIO

NDC 43742-1325-1

HOMEOPATHIC

RHEUMAGESIC

1 FL OZ (30 ml)